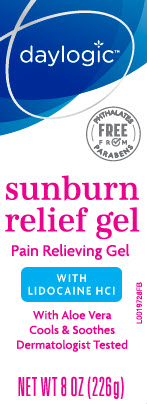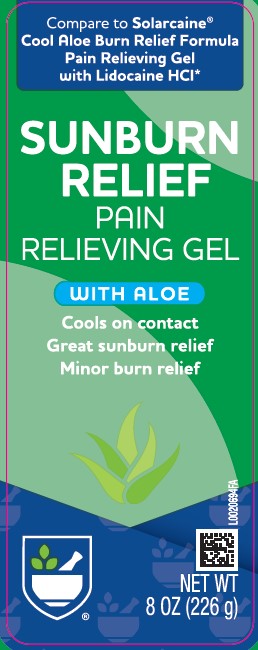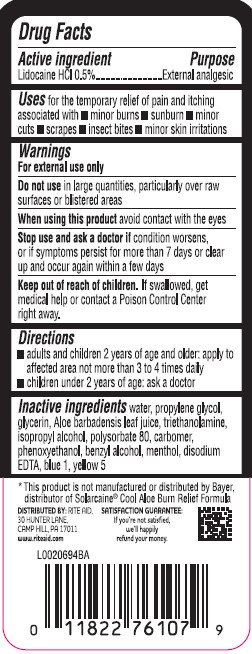 DRUG LABEL: Sunburn Relief
NDC: 11822-0776 | Form: GEL
Manufacturer: Rite Aid Corporation
Category: otc | Type: HUMAN OTC DRUG LABEL
Date: 20260130

ACTIVE INGREDIENTS: LIDOCAINE HYDROCHLORIDE 5 mg/1 g
INACTIVE INGREDIENTS: WATER; PROPYLENE GLYCOL; GLYCERIN; ALOE VERA LEAF; TROLAMINE; ISOPROPYL ALCOHOL; POLYSORBATE 80; CARBOMER HOMOPOLYMER, UNSPECIFIED TYPE; PHENOXYETHANOL; BENZYL ALCOHOL; MENTHOL; EDETATE DISODIUM ANHYDROUS; FD&C BLUE NO. 1; FD&C YELLOW NO. 5

Rite Aid_Daylogic 005.002/005AC-AD
Sunburn Relief Gel

Active ingredient

Lidocaine HCl 0.5%

Purpose

External analgesic

Use

for the temporary relief of pain and itching associated with

- minor burns
- sunburn
- minor cuts
- scrapes
- insect bites
- minor skin irritations

Warnings

For external use only

Do not use

in large quantities, particularly over raw surfaces or blistered areas

When using this product

avoid contact with the eyes

Stop use and ask a doctor if

condition worsens, or if symptoms persist for more than 7 days or clear up and occur again within a few days

Keep out of reach of children.

If swallowed, get medical help or contact a Poison Control Center right away.

Directions

- adults and children 2 years of age and older: apply to affected area not more than 3 to 4 times daily
- children under 2 years of age: ask a doctor

Inactive ingredients

water, propylene glycol, glycerin, Aloe barbadensis leaf juice, triethanolamine, isopropyl alcohol, polysorbate 80, carbomer, phenoxyethanol, benzyl alcohol, menthol, disodium EDTA, blue 1, yellow 5

ADVERSE REACTION

*This product is not manufactured or distributed by Bayer, distributer of Solarcaine®Cool Aloe Burn Relief Formula

DISTRIBUTED BY: RITE AID

30 HUNTER LANE

CAMP HILL, PA 17011

www.riteaid.com

SATISFACTION GUARANTEE:

If you're not satisfied, we'll happily refund your money.

Principal Panel Display

Compare to Salarcaine®Cool Aloe Burn Relief Formula Pain Relieving Gel with Lidocaine HCI*

SUNBURN

RELIEF

PAIN RELIEVING GEL

WITH ALOE

Cools on contact

Great sunburn relief

Minor burn relief

NET WT 8 OZ (226 g)

Principal Panel Display

daylogic™

daylogic

FREE FROM PHTHALATES & PARABENS

sunburn relief gel

Pain Relieving Gel

WITH LIDOCAINE HCI

With Aloe Vera

Cools & Sooothes

Dermatologist Tested

NET WT 8 OZ (226g)